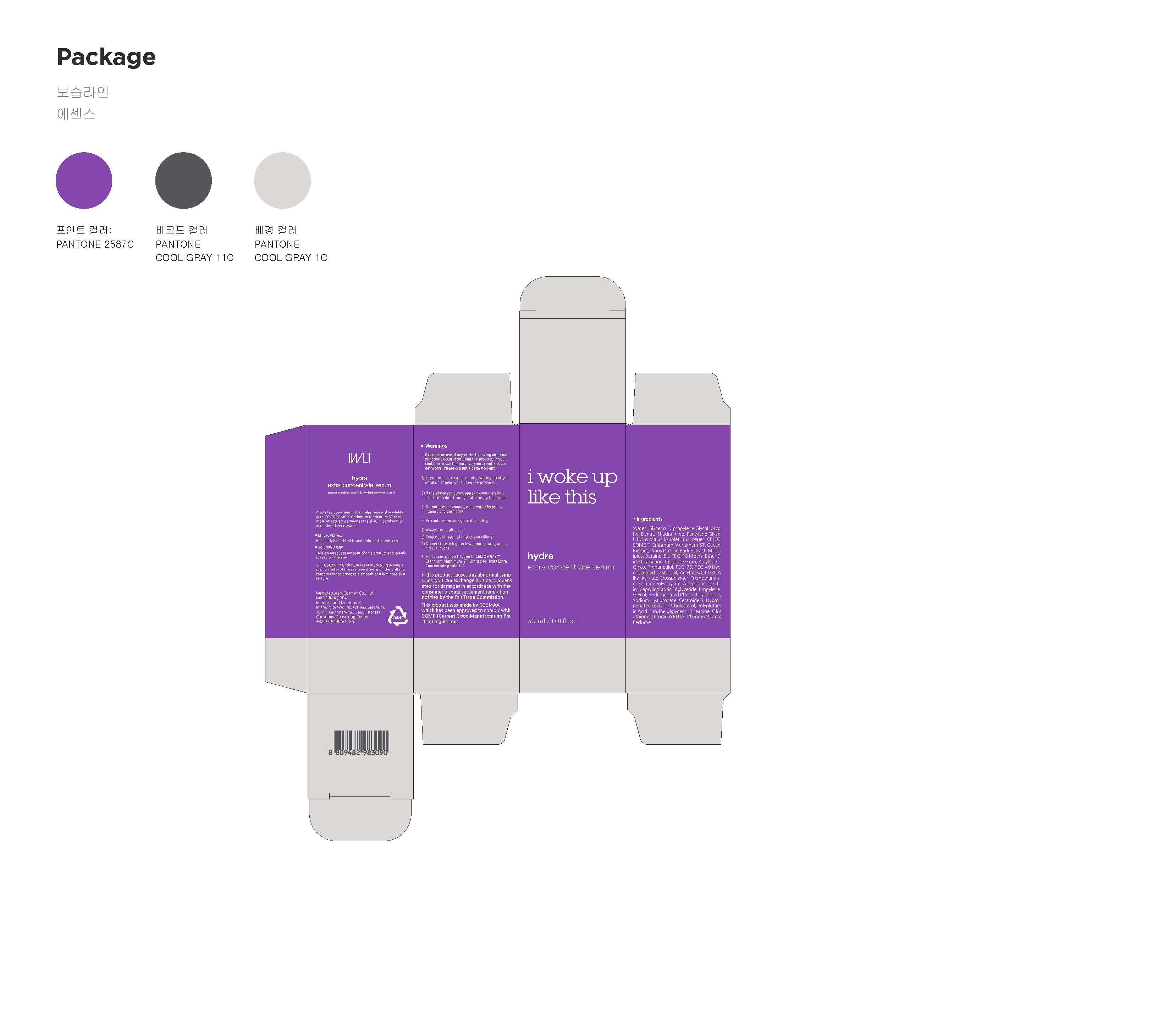 DRUG LABEL: Hydra Extra ConcentrateSerum
NDC: 71217-0004 | Form: LIQUID
Manufacturer: In This Morning
Category: otc | Type: HUMAN OTC DRUG LABEL
Date: 20170213

ACTIVE INGREDIENTS: ADENOSINE 0.04 g/100 mL; NIACINAMIDE 2 g/100 mL
INACTIVE INGREDIENTS: WATER; GLYCERIN; BUTYLENE GLYCOL

Drug Facts

ACTIVE INGREDIENT

Niacinamide, Adenosine

INACTIVE INGREDIENT

Water, Glycerin, Butylene Glycol, Crithmum Maritimum Callus Culture Filtrate, etc.

PURPOSE

Helps brighten the skin and reduce skin wrinkles.

keep out or reach of the children

INDICATIONS AND USAGE

Take an adequate amount of this product and evenly spread on the skin.

WARNINGS

1. Discontinue use, if any of the following abnormal symptoms
occur after using the product. If you continue to use the
product, your symptoms can get worse. Please consult a
dermatologist.
1) If symptoms such as red spots, swelling, itching or irritation appear while
using the product
2) If the above symptoms appear when the skin is exposed to direct sunlight
after using the product
2. Do not use on wounds, and areas affected by eczema and
dermatitis
3. Precautions for storage and handling
1) Always recap after use.
2) Keep out of reach of infants and children.
3) Do not store at high or low temperatures, and in direct sunlight.
4. Avoid contact with the eyes.
- If you are very sensitive to a sticking plaster or a wet compress, use with
caution or discontinue use
- Limited to Whitening Concentrate Treatment Mask products.
- Fine grains can be felt due to CELTOSOME™ Crithmum Maritimum ST (Limited
to Hydra Extra Concentrate products.)
5. The SPF of this product was measured according to the
method of Cosmmedics Europe and its PA according to the
method of the Japan Cosmetic Industry Association (JCIA).
(Limited to Protective Base Sunscreen products for dry skin)
6. The SPF of this product was measured according to the
International SPF Test Method and its PA according to the
method of the Japan Cosmetic Industry Association (JCIA).
(Limited to Protective Base Sunscreen products for oily skin)
7. The SPF and PA of this product were measured according
to the methods proposed by the Regulations of Functional
Cosmetic Evaluation. (Limited to BB cream.)
8. Do not use on children under the age of 3 because this
product contains salicylic acids and salts.
(Limited to Purifying Sebum Relief Spot products.)
If this product causes any abnormal symptoms,
you can exchange it or be compensated for damages in
accordance with the consumer dispute settlement regulation
notified by the Fair Trade Commission.
This product was made by COSMAX
which has been approved to comply with
CGMP (Current Good Manufacturing Practice) regulations.

DOSAGE AND ADMINISTRATION

for external use only